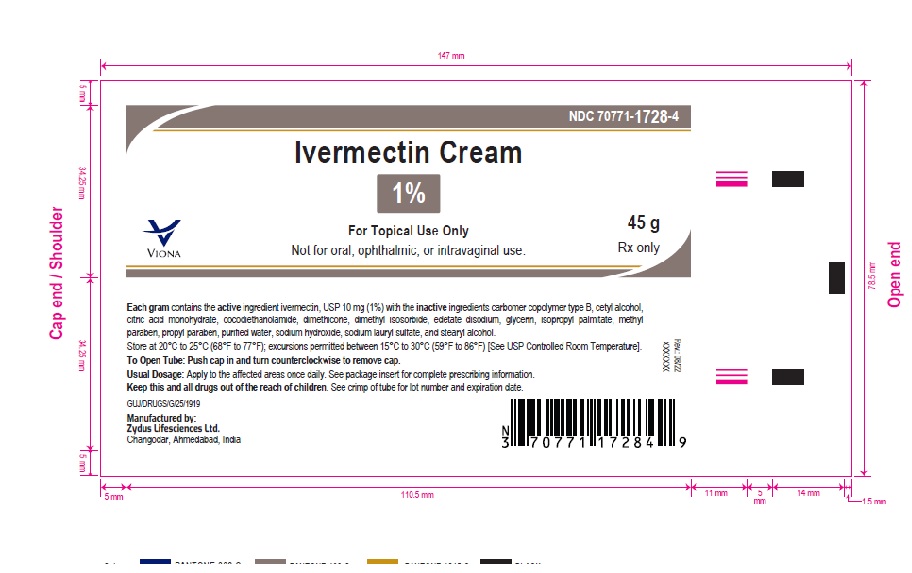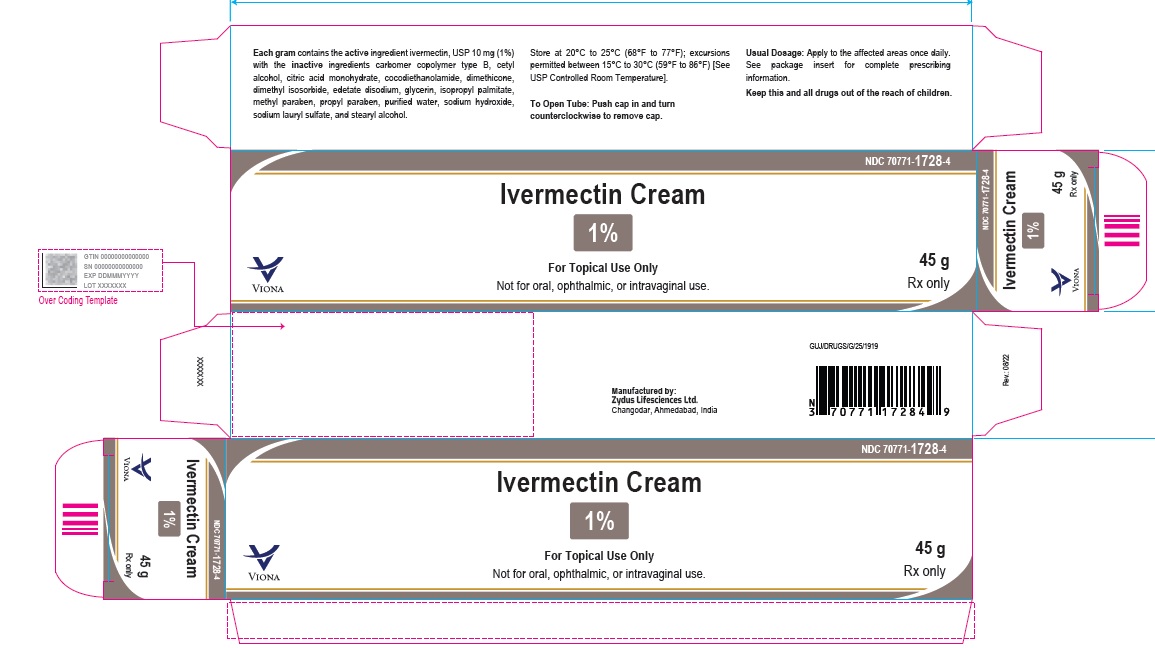 DRUG LABEL: ivermectin
NDC: 70771-1728 | Form: CREAM
Manufacturer: Zydus Lifesciences Limited
Category: prescription | Type: HUMAN PRESCRIPTION DRUG LABEL
Date: 20230607

ACTIVE INGREDIENTS: IVERMECTIN 10 mg/1 g
INACTIVE INGREDIENTS: CARBOMER COPOLYMER TYPE B (ALLYL PENTAERYTHRITOL CROSSLINKED); CETYL ALCOHOL; CITRIC ACID MONOHYDRATE; COCO DIETHANOLAMIDE; DIMETHICONE; DIMETHYL ISOSORBIDE; EDETATE DISODIUM; GLYCERIN; ISOPROPYL PALMITATE; METHYLPARABEN; PROPYLPARABEN; SODIUM HYDROXIDE; SODIUM LAURYL SULFATE; STEARYL ALCOHOL; WATER

Ivermectin Cream

PACKAGE LABEL.PRINCIPAL DISPLAY PANEL

Ivermectin Cream, 1%

45 gm

NDC 70771-1728-4

Rx only